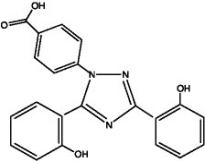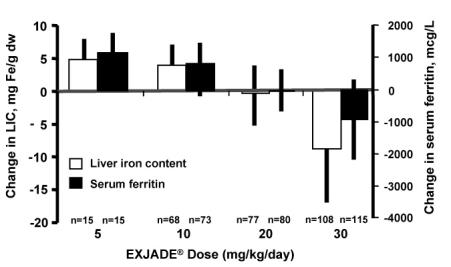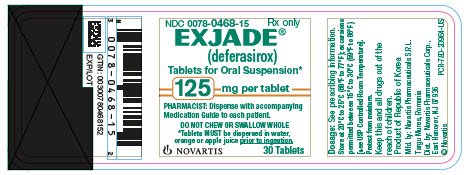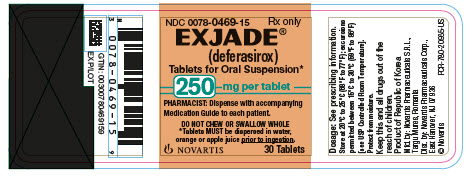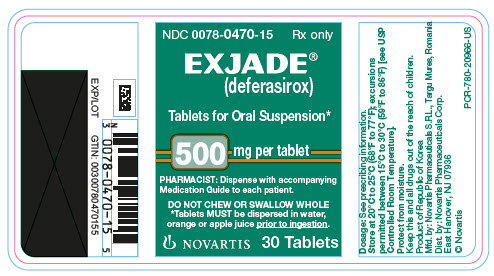 DRUG LABEL: Exjade
NDC: 0078-0468 | Form: TABLET, FOR SUSPENSION
Manufacturer: Novartis Pharmaceuticals Corporation
Category: prescription | Type: HUMAN PRESCRIPTION DRUG LABEL
Date: 20260128

ACTIVE INGREDIENTS: DEFERASIROX 125 mg/1 1
INACTIVE INGREDIENTS: CROSPOVIDONE; LACTOSE MONOHYDRATE; MAGNESIUM STEARATE; CELLULOSE, MICROCRYSTALLINE; POVIDONE K30; SILICON DIOXIDE; SODIUM LAURYL SULFATE

HIGHLIGHTS OF PRESCRIBING INFORMATION

These highlights do not include all the information needed to use EXJADE safely and effectively. See full prescribing information for EXJADE.
EXJADE® (deferasirox) tablets, for oral suspension
Initial U.S. Approval: 2005

WARNING: RENAL FAILURE, HEPATIC FAILURE, and GASTROINTESTINAL HEMORRHAGE

See full prescribing information for complete boxed warning.

Exjade may cause:

- acute kidney injury, including acute renal failure requiring dialysis and renal tubular toxicity including Fanconi syndrome (5.1)
- hepatic toxicity, including failure (5.2)
- gastrointestinal hemorrhage (5.3)

Exjade therapy requires close patient monitoring, including laboratory tests of renal and hepatic function. (5)

RECENT MAJOR CHANGES

Indications and Usage, Limitations of Use (1.3) | 7/2019

1 INDICATIONS AND USAGE

Exjade is an iron chelator indicated for the treatment of chronic iron overload due to blood transfusions in patients 2 years of age and older. (1.1)

Exjade is indicated for the treatment of chronic iron overload in patients 10 years of age and older with non-transfusion-dependent thalassemia (NTDT) syndromes, and with a liver iron (Fe) concentration (LIC) of at least 5 mg Fe per gram of dry weight and a serum ferritin greater than 300 mcg/L. (1.2)

Limitations of Use:

The safety and efficacy of Exjade when administered with other iron chelation therapy have not been established. (1.3)

2 DOSAGE AND ADMINISTRATION

- Transfusional Iron Overload: Initial dose for patients with estimated glomerular filtration rate (eGFR) greater than 60 mL/min/1.73 m^2 is 20 mg per kg body weight once daily, as oral suspension. Calculate dose to the nearest whole tablet. (2.1)
- NTDT Syndromes: Initial dose for patients with eGFR greater than 60 mL/min/1.73 m^2 is 10 mg per kg body weight once daily, as oral suspension. Calculate dose to the nearest whole tablet. (2.2)

3 DOSAGE FORMS AND STRENGTHS

Tablets for oral suspension: 125 mg, 250 mg, 500 mg. (3)

4 CONTRAINDICATIONS

- Estimated GFR less than 40 mL/min/1.73 m^2. (4)
- Patients with poor performance status. (4)
- Patients with high-risk myelodysplastic syndrome (MDS). (4)
- Patients with advanced malignancies. (4)
- Patients with platelet counts less than 50 x 10^9/L. (4)
- Known hypersensitivity to deferasirox or any component of Exjade. (4)

5 WARNINGS AND PRECAUTIONS

- Acute Kidney Injury: Measure serum creatinine in duplicate before starting therapy. Monitor renal function during Exjade therapy and reduce dose or interrupt therapy for toxicity. (2.1, 2.4, 5.1)
- Hepatic Toxicity: Monitor hepatic function. Reduce dose or interrupt therapy for toxicity. (5.2)
- Fatal and Nonfatal Gastrointestinal Bleeding, Ulceration, and Irritation: Risk may be greater in patients who are taking Exjade in combination with drugs that have known ulcerogenic or hemorrhagic potential. (5.3)
- Bone Marrow Suppression: Neutropenia, agranulocytosis, worsening anemia, and thrombocytopenia, including fatal events; monitor blood counts during Exjade therapy. Interrupt therapy for toxicity. (5.4)
- Age-related Risk of Toxicity: Monitor elderly and pediatric patients closely for toxicity. (5.5)
- Hypersensitivity Reactions: Discontinue Exjade for severe reactions and institute medical intervention. (5.7)
- Severe Skin Reactions, including Stevens-Johnson syndrome (SJS), toxic epidermal necrolysis (TEN), and Drug Reaction with Eosinophilia and Systemic Symptoms (DRESS): Discontinue Exjade. (5.8)

6 ADVERSE REACTIONS

In patients with transfusional iron overload, the most frequently occurring (greater than 5%) adverse reactions are diarrhea, vomiting, nausea, abdominal pain, skin rashes, and increases in serum creatinine. In Exjade-treated patients with NTDT syndromes, the most frequently occurring (greater than 5%) adverse reactions are diarrhea, rash, and nausea. (6.1)

To report SUSPECTED ADVERSE REACTIONS, contact Novartis Pharmaceuticals Corporation at 1-888-669-6682 or FDA at 1-800-FDA-1088 or www.fda.gov/medwatch.

7 DRUG INTERACTIONS

- Do not take Exjade with aluminum-containing antacid preparations. (7.1)
- Exjade increases the exposure of the CYP2C8 substrate repaglinide. Consider repaglinide dose reduction and monitor blood glucose levels. (7.3)
- Avoid the use of Exjade with CYP1A2 substrate theophylline. (7.4)
- Deferasirox increases exposure of busulfan. Monitor plasma concentrations of busulfan when coadministered with deferasirox to allow dose adjustment of busulfan as needed. (7.7)

8 USE IN SPECIFIC POPULATIONS

Lactation: Advise women not to breastfeed. (8.2)

FULL PRESCRIBING INFORMATION

WARNING: RENAL FAILURE, HEPATIC FAILURE, and GASTROINTESTINAL HEMORRHAGE

Renal Failure

- Exjade can cause acute renal failure and death, particularly in patients with comorbidities and those who are in the advanced stages of their hematologic disorders.
- Evaluate baseline renal function prior to starting or increasing Exjade dosing in all patients. Exjade is contraindicated in adult and pediatric patients with eGFR less than 40 mL/min/1.73 m^2. Measure serum creatinine in duplicate prior to initiation of therapy. Monitor renal function at least monthly. For patients with baseline renal impairment or increased risk of acute renal failure, monitor renal function weekly for the first month, then at least monthly. Reduce the starting dose in patients with preexisting renal disease. During therapy, increase the frequency of monitoring and modify the dose for patients with an increased risk of renal impairment, including use of concomitant nephrotoxic drugs, and pediatric patients with volume depletion or overchelation [see Dosage and Administration (2.1, 2.4, 2.5), Warnings and Precautions (5.1), Adverse Reactions (6.1, 6.2)].

Hepatic Failure

- Exjade can cause hepatic injury including hepatic failure and death.
- Measure serum transaminases and bilirubin in all patients prior to initiating treatment, every 2 weeks during the first month, and at least monthly thereafter.
- Avoid use of Exjade in patients with severe (Child-Pugh C) hepatic impairment and reduce the dose in patients with moderate (Child-Pugh B) hepatic impairment [see Dosage and Administration (2.4), Warnings and Precautions (5.2)].

Gastrointestinal Hemorrhage

- Exjade can cause gastrointestinal (GI) hemorrhages, which may be fatal, especially in elderly patients who have advanced hematologic malignancies and/or low platelet counts.
- Monitor patients and discontinue Exjade for suspected GI ulceration or hemorrhage [see Warnings and Precautions (5.3)].

1 INDICATIONS AND USAGE

1.1 Treatment of Chronic Iron Overload Due to Blood Transfusions (Transfusional Iron Overload)

Exjade is indicated for the treatment of chronic iron overload due to blood transfusions (transfusional hemosiderosis) in patients 2 years of age and older.

1.2 Treatment of Chronic Iron Overload in Non-Transfusion-Dependent Thalassemia Syndromes

Exjade is indicated for the treatment of chronic iron overload in patients 10 years of age and older with non-transfusion-dependent thalassemia (NTDT) syndromes and with a liver iron concentration (LIC) of at least 5 milligrams of iron per gram of liver dry weight (mg Fe/g dw) and a serum ferritin greater than 300 mcg/L.

1.3 Limitations of Use

The safety and efficacy of Exjade when administered with other iron chelation therapy have not been established.

2 DOSAGE AND ADMINISTRATION

2.1 Transfusional Iron Overload

Exjade therapy should only be considered when a patient has evidence of chronic transfusional iron overload. The evidence should include the transfusion of at least 100 mL/kg of packed red blood cells (e.g., at least 20 units of packed red blood cells for a 40 kg person or more in individuals weighing more than 40 kg), and a serum ferritin consistently greater than 1,000 mcg/L.

Prior to starting therapy or increasing dose, evaluate:

- Serum ferritin level
- Baseline renal function:
  - Obtain serum creatinine in duplicate (due to variations in measurements) to establish accurate baseline
  - Calculate the estimated glomerular filtration rate (eGFR). Use a prediction equation appropriate for adult patients (e.g., CKD-EPI, MDRD method) and in pediatric patients (e.g., Schwartz equations).
  - Obtain urinalyses and serum electrolytes to evaluate renal tubular function [see Dosage and Administration (2.4), Warnings and Precautions (5.1)].
- Serum transaminases and bilirubin [see Dosage and Administration (2.4), Warnings and Precautions (5.2)]
- Baseline auditory and ophthalmic examinations [see Warnings and Precautions (5.10)]

Initiating Therapy:

The recommended initial dose of Exjade for patients 2 years of age and older with eGFR greater than 60 mL/min/1.73 m^2 is 20 mg per kg body weight orally, once daily. Calculate doses (mg per kg per day) to the nearest whole tablet.

During Therapy:

- Monitor serum ferritin monthly and adjust the dose of Exjade, if necessary, every 3-6 months based on serum ferritin trends.
- Use the minimum effective dose to achieve a trend of decreasing ferritin.
- Make dose adjustments in steps of 5 or 10 mg per kg and tailor adjustments to the individual patient’s response and therapeutic goals.
- In patients not adequately controlled with doses of 30 mg per kg (e.g., serum ferritin levels persistently above 2,500 mcg/L and not showing a decreasing trend over time), doses of up to 40 mg per kg may be considered. Doses above 40 mg per kg are not recommended [see Warnings and Precautions (5.6)].
- Adjust dose based on serum ferritin levels
  - If the serum ferritin falls below 1,000 mcg/L at 2 consecutive visits, consider dose reduction, especially if the dose is greater than 25 mg/kg/day [see Adverse Reactions (6.1)].
  - If the serum ferritin falls below 500 mcg/L, interrupt Exjade to minimize the risk of overchelation, and continue monthly monitoring [see Warnings and Precautions (5.6)].
  - Evaluate the need for ongoing chelation therapy for patients whose conditions no longer require regular blood transfusions.
  - Use the minimum effective dose to maintain iron burden in the target range [see Warnings and Precautions (5.6)].
- Monitor blood counts, liver function, renal function and ferritin monthly [see Warnings and Precautions (5.1, 5.2, 5.4)].
- Interrupt Exjade for pediatric patients who have acute illnesses, which can cause volume depletion, such as vomiting, diarrhea, or prolonged decreased oral intake, and monitor more frequently. Resume therapy as appropriate, based on assessments of renal function, when oral intake and volume status are normal [see Dosage and Administration (2.4, 2.5), Warnings and Precautions (5.1), Use in Specific Populations (8.4), Clinical Pharmacology (12.3)].

2.2 Iron Overload in Non-Transfusion-Dependent Thalassemia Syndromes

Exjade therapy should only be considered when a patient with NTDT syndrome has an LIC of at least 5 mg Fe/g dw and a serum ferritin greater than 300 mcg/L.

Prior to starting therapy, obtain:

- LIC by liver biopsy or by an FDA-cleared or approved method for identifying patients for treatment with deferasirox therapy
- Serum ferritin level on at least 2 measurements 1-month apart [see Clinical Studies (14)]
- Baseline renal function:
  - Obtain serum creatinine in duplicate (due to variations in measurements) to establish accurate baseline
  - Calculate eGFR. Use a prediction equation appropriate for adult patients (e.g., CKD-EPI, MDRD method) and in pediatric patients (e.g., Schwartz equations).
  - Obtain urinalyses and serum electrolytes to evaluate renal tubular function [see Dosage and Administration (2.4), Warnings and Precautions (5.1)].
- Serum transaminases and bilirubin [see Dosage and Administration (2.4), Warnings and Precautions (5.2)]
- Baseline auditory and ophthalmic examinations [see Warnings and Precautions (5.10)]

Initiating Therapy:

- The recommended initial dose of Exjade for patients with eGFR greater than 60 mL/min/1.73 m^2 is 10 mg per kg body weight orally once daily. Calculate doses (mg per kg per day) to the nearest whole tablet.
- If the baseline LIC is greater than 15 mg Fe/g dw, consider increasing the dose to 20 mg/kg/day after 4 weeks.

During Therapy:

- Monitor serum ferritin monthly to assess the patient’s response to therapy and to minimize the risk of overchelation [see Warnings and Precautions (5.6)]. Interrupt treatment when serum ferritin is less than 300 mcg/L and obtain an LIC to determine whether the LIC has fallen to less than 3 mg Fe/g dw.
- Use the minimum effective dose to achieve a trend of decreasing ferritin.
- Monitor LIC every 6 months.
- After 6 months of therapy, if the LIC remains greater than 7 mg Fe/g dw, increase the dose of deferasirox to a maximum of 20 mg/kg/day. Do not exceed a maximum of 20 mg/kg/day.
- If after 6 months of therapy, the LIC is 3-7 mg Fe/g dw, continue treatment with deferasirox at no more than 10 mg/kg/day.
- When the LIC is less than 3 mg Fe/g dw, interrupt treatment with deferasirox and continue to monitor the LIC.
- Monitor blood counts, liver function, renal function and ferritin monthly [see Warnings and Precautions (5.1, 5.2, 5.4)].
- Increase monitoring frequency for pediatric patients who have acute illness, which can cause volume depletion, such as vomiting, diarrhea, or prolonged decreased oral intake. Consider dose interruption until oral intake and volume status are normal [see Dosage and Administration (2.4, 2.5), Warnings and Precautions (5.1), Use in Specific Populations (8.4), Clinical Pharmacology (12.3)].

Restart treatment when the LIC rises again to more than 5 mg Fe/g dw.

2.3 Administration

Do not chew tablets or swallow them whole.

Take Exjade once daily on an empty stomach at least 30 minutes before food, preferably at the same time each day. Completely disperse tablets by stirring in water, orange juice, or apple juice until a fine suspension is obtained. Disperse doses of less than 1 g in 3.5 ounces of liquid and doses of 1 g or greater in 7 ounces of liquid. After swallowing the suspension, resuspend any residue in a small volume of liquid and swallow. Do not take Exjade with aluminum-containing antacid products [see Drug Interactions (7.1)].

2.4 Use in Patients With Baseline Hepatic or Renal Impairment

Patients with Baseline Hepatic Impairment

Mild (Child-Pugh A) Hepatic Impairment: No dose adjustment is necessary.

Moderate (Child-Pugh B) Hepatic Impairment: Reduce the starting dose by 50%.

Severe (Child-Pugh C) Hepatic Impairment: Avoid Exjade [see Warnings and Precautions (5.2), Use in Specific Populations (8.7)].

Patients with Baseline Renal Impairment

Do not use Exjade in adult or pediatric patients with eGFR less than 40 mL/min/1.73 m^2 [see Dosage and Administration (2.5), Contraindications (4)].

For patients with renal impairment (eGFR 40-60 mL/min/1.73 m^2), reduce the starting dose by 50% [see Use in Specific Populations (8.6)].

Exercise caution in pediatric patients with eGFR between 40 and 60 mL/min/1.73 m^2. If treatment is needed, use the minimum effective dose and monitor renal function frequently. Individualize dose titration based on improvement in renal injury [see Use in Specific Populations (8.6)].

2.5 Dose Modifications for Decreases in Renal Function While on Exjade

Exjade is contraindicated in patients with eGFR less than 40 mL/min/1.73 m^2 [see Contraindications (4)].

For decreases in renal function while receiving Exjade [see Warnings and Precautions (5.1)], modify the dose as follows:

Transfusional Iron Overload

Adults:

- If the serum creatinine increases by 33% or more above the average baseline measurement, repeat the serum creatinine within 1 week, and if still elevated by 33% or more, reduce the dose by 10 mg per kg.

Pediatric Patients (ages 2 years–17 years):

- Reduce the dose by 10 mg/kg/day if eGFR decreases by greater than 33% below the average baseline measurement and repeat the eGFR within 1 week.
- Interrupt Exjade for acute illnesses, which can cause volume depletion, such as vomiting, diarrhea, or prolonged decreased oral intake, and monitor more frequently. Resume therapy as appropriate, based on assessments of renal function, when oral intake and volume status are normal. Avoid use of other nephrotoxic drugs [see Warnings and Precautions (5.1)].
- In the setting of decreased renal function, evaluate the risk benefit profile of continued Exjade use. Use the minimum effective Exjade dose and monitor renal function more frequently, by evaluating tubular and glomerular function. Titrate dosing based on renal injury. Consider dose reduction or interruption and less nephrotoxic therapies until improvement of renal function. If signs of renal tubular or glomerular injury occur in the presence of other risk factors such as volume depletion, reduce or interrupt Exjade to prevent severe and irreversible renal injury [see Warnings and Precautions (5.1)].

All Patients (regardless of age):

- Discontinue therapy for eGFR less than 40 mL/min/1.73 m^2 [see Contraindications (4)].

Non-Transfusion-Dependent Thalassemia Syndromes

Adults:

- If the serum creatinine increases by 33% or more above the average baseline measurement, repeat the serum creatinine within 1 week, and if still elevated by 33% or more, interrupt therapy if the dose is 5 mg per kg, or reduce by 50% if the dose is 10 or 20 mg per kg.

Pediatric Patients (ages 10 years–17 years):

- Reduce the dose by 5 mg/kg/day if eGFR decreases by greater than 33% below the average baseline measurement and repeat the eGFR within 1 week.
- Increase monitoring frequency for pediatric patients who have acute illnesses, which can cause volume depletion, such as vomiting, diarrhea, or prolonged decreased oral intake. Consider dose interruption until oral intake and volume status are normal. Avoid use of other nephrotoxic drugs [see Warnings and Precautions (5.1)].
- In the setting of decreased renal function, evaluate the risk benefit profile of continued Exjade use. Use the minimum effective Exjade dose and monitor renal function more frequently, by evaluating tubular and glomerular function. Titrate dosing based on renal injury. Consider dose reduction or interruption and less nephrotoxic therapies until improvement of renal function. If signs of renal tubular or glomerular injury occur in the presence of other risk factors such as volume depletion, reduce or interrupt Exjade to prevent severe and irreversible renal injury [see Warnings and Precautions (5.1)].

All Patients (regardless of age):

- Discontinue therapy for eGFR less than 40 mL/min/1.73 m^2 [see Contraindications (4)].

2.6 Dose Modifications Based on Concomitant Medications

UDP-glucuronosyltransferases (UGT) Inducers

Concomitant use of UGT inducers decreases Exjade systemic exposure. Avoid the concomitant use of potent UGT inducers (e.g., rifampicin, phenytoin, phenobarbital, ritonavir) with Exjade. If you must administer Exjade with 1 of these agents, consider increasing the initial dose of Exjade by 50%, and monitor serum ferritin levels and clinical responses for further dose modification [see Dosage and Administration (2.1, 2.2), Drug Interactions (7.5)].

Bile Acid Sequestrants

Concomitant use of bile acid sequestrants decreases Exjade systemic exposure. Avoid the concomitant use of bile acid sequestrants (e.g., cholestyramine, colesevelam, colestipol) with Exjade. If you must administer Exjade with 1 of these agents, consider increasing the initial dose of Exjade by 50%, and monitor serum ferritin levels and clinical responses for further dose modification [see Dosage and Administration (2.1, 2.2), Drug Interactions (7.6)].

3 DOSAGE FORMS AND STRENGTHS

- 125 mg tablets
  Off-white, round, flat tablet with beveled edge and imprinted with “J” and “125” on one side and “NVR” on the other.
- 250 mg tablets
  Off-white, round, flat tablet with beveled edge and imprinted with “J” and “250” on one side and “NVR” on the other.
- 500 mg tablets
  Off-white, round, flat tablet with beveled edge and imprinted with “J” and “500” on one side and “NVR” on the other.

4 CONTRAINDICATIONS

Exjade is contraindicated in patients with:

- Estimated GFR less than 40 mL/min/1.73 m^2 [see Dosage and Administration (2.5), Warnings and Precautions (5.1)];
- Poor performance status; [see Warnings and Precautions (5.1, 5.3)]
- High-risk myelodysplastic syndromes; (this patient population was not studied and is not expected to benefit from chelation therapy)
- Advanced malignancies. [see Warnings and Precautions (5.1, 5.3)]
- Platelet counts less than 50 x 10^9/L [see Warnings and Precautions (5.3, 5.4)
- Known hypersensitivity to deferasirox or any component of Exjade [see Warnings and Precautions (5.7), Adverse Reactions (6.2)].

5 WARNINGS AND PRECAUTIONS

5.1 Acute Kidney Injury, Including Acute Renal Failure Requiring Dialysis, and Renal Tubular Toxicity Including Fanconi Syndrome

Exjade is contraindicated in patients with eGFR less than 40 mL/min/1.73 m^2. Exercise caution in pediatric patients with eGFR between 40 and 60 mL/minute/1.73 m^2. If treatment is needed, use the minimum effective dose and monitor renal function frequently. Individualize dose titration based on improvement in renal injury [see Use in Specific Populations (8.6)]. For patients with renal impairment (eGFR 40–60 mL/min/1.73 m^2), reduce the starting dose by 50% [see Dosage and Administration (2.4, 2.5), Use in Specific Populations (8.6)].

Exjade can cause acute kidney injury including renal failure requiring dialysis that has resulted in fatal outcomes. Based on postmarketing experience, most fatalities have occurred in patients with multiple comorbidities and who were in advanced stages of their hematological disorders. In the clinical trials, adult and pediatric Exjade-treated patients with no preexisting renal disease experienced dose-dependent mild, non-progressive increases in serum creatinine and proteinuria. Preexisting renal disease and concomitant use of other nephrotoxic drugs may increase the risk of acute kidney injury in adult and pediatric patients. Acute illnesses associated with volume depletion and overchelation may increase the risk of acute kidney injury in pediatric patients. In pediatric patients, small decreases in eGFR can result in increases in Exjade exposure, particularly in younger patients with body surface area typical of patients less than age 7 years. This can lead to a cycle of worsening renal function and further increases in Exjade exposure, unless the dose is reduced or interrupted. Renal tubular toxicity, including acquired Fanconi syndrome, has been reported in patients treated with Exjade, most commonly in pediatric patients with beta-thalassemia and serum ferritin levels less than 1,500 mcg/L [see Warnings and Precautions (5.6), Adverse Reactions (6.1, 6.2), Use in Specific Populations (8.4), Clinical Pharmacology (12.3)].

Evaluate renal glomerular and tubular function before initiating therapy or increasing the dose. Use prediction equations validated for use in adult and pediatric patients to estimate GFR. Obtain serum electrolytes and urinalysis in all patients to evaluate renal tubular function [see Dosage and Administration (2.1, 2.2)].

Monitor all patients for changes in eGFR and for renal tubular toxicity weekly during the first month after initiation or modification of therapy and at least monthly thereafter. Dose reduction or interruption may be considered if abnormalities occur in levels of markers of renal tubular function and/or as clinically indicated. Monitor serum ferritin monthly to evaluate for overchelation. Use the minimum dose to establish and maintain a low iron burden. Monitor renal function more frequently in patients with preexisting renal disease or decreased renal function. In pediatric patients, interrupt Exjade during acute illnesses, which can cause volume depletion, such as vomiting, diarrhea, or prolonged decreased oral intake, and monitor renal function more frequently. Promptly correct fluid deficits to prevent renal injury. Resume therapy as appropriate, based on assessments of renal function, when oral intake and volume status are normal [see Dosage and Administration (2.5), Warnings and Precautions (5.6), Adverse Reactions (6.1, 6.2), Use in Specific Populations (8.4)].

5.2 Hepatic Toxicity and Failure

Exjade can cause hepatic injury, fatal in some patients. In Study 1, 4 patients (1.3%) discontinued Exjade because of hepatic toxicity (drug-induced hepatitis in 2 patients and increased serum transaminases in 2 additional patients). Hepatic toxicity appears to be more common in patients greater than 55 years of age. Hepatic failure was more common in patients with significant comorbidities, including liver cirrhosis and multi-organ failure [see Adverse Reactions (6.1)]. Acute liver injury and failure, including fatal outcomes, have occurred in pediatric Exjade-treated patients. Liver failure occurred in association with acute kidney injury in pediatric patients at risk for overchelation during a volume depleting event. Interrupt Exjade therapy when acute liver injury or acute kidney injury is suspected and during volume depletion. Monitor liver and renal function more frequently in pediatric patients who are receiving Exjade in the 20-40 mg/kg/day range and when iron burden is approaching normal. Use the minimum effective dose to achieve and maintain a low iron burden [see Dosage and Administration (2.5), Warnings and Precautions (5.6), Adverse Reactions (6.1)].

Measure transaminases [aspartate transaminase (AST) and alanine transaminase (ALT)] and bilirubin in all patients before the initiation of treatment, and every 2 weeks during the first month and at least monthly thereafter. Consider dose modifications or interruption of treatment for severe or persistent elevations.

Avoid the use of Exjade in patients with severe (Child-Pugh C) hepatic impairment. Reduce the starting dose in patients with moderate (Child-Pugh B) hepatic impairment [see Dosage and Administration (2.4), Use in Specific Populations (8.7)]. Patients with mild (Child-Pugh A) or moderate (Child-Pugh B) hepatic impairment may be at higher risk for hepatic toxicity.

5.3 Gastrointestinal (GI) Ulceration, Hemorrhage, and Perforation

GI hemorrhage, including deaths, has been reported in Exjade-treated patients, especially in elderly patients who had advanced hematologic malignancies and/or low platelet counts. Nonfatal upper GI irritation, ulceration and hemorrhage have been reported in patients, including children and adolescents, receiving Exjade [see Adverse Reactions (6.1)]. Monitor for signs and symptoms of GI ulceration and hemorrhage during Exjade therapy and promptly initiate additional evaluation and treatment if a serious GI adverse reaction is suspected. The risk of GI hemorrhage may be increased when administering Exjade in combination with drugs that have ulcerogenic or hemorrhagic potential, such as nonsteroidal anti-inflammatory drugs (NSAIDs), corticosteroids, oral bisphosphonates, or anticoagulants. There have been reports of ulcers complicated with GI perforation (including fatal outcome) [see Adverse Reactions (6.2)].

5.4 Bone Marrow Suppression

Neutropenia, agranulocytosis, worsening anemia, and thrombocytopenia, including fatal events, have been reported in patients treated with Exjade. Preexisting hematologic disorders may increase this risk. Monitor blood counts in all patients. Interrupt treatment with Exjade in patients who develop cytopenias until the cause of the cytopenia has been determined. Exjade is contraindicated in patients with platelet counts below 50 x 10^9/L.

5.5 Age-Related Risk of Toxicity

Elderly Patients

Exjade has been associated with serious and fatal adverse reactions in the postmarketing setting among adults, predominantly in elderly patients. Monitor elderly patients treated with Exjade more frequently for toxicity [see Use in Specific Populations (8.5)].

Pediatric Patients

Exjade has been associated with serious and fatal adverse reactions in pediatric patients in the postmarketing setting. These events were frequently associated with volume depletion or with continued Exjade doses in the 20-40 mg/kg/day range when body iron burden was approaching or in the normal range. Interrupt Exjade in patients with volume depletion, and resume Exjade when renal function and fluid volume have normalized. Monitor liver and renal function more frequently during volume depletion and in patients receiving Exjade in the 20-40 mg/kg/day range when iron burden is approaching the normal range. Use the minimum effective dose to achieve and maintain a low iron burden [see Dosage and Administration (2.4), Warnings and Precautions (5.6), Use in Specific Populations (8.4)].

5.6 Overchelation

For patients with transfusional iron overload, measure serum ferritin monthly to assess the patient’s response to therapy and minimize the risk of overchelation. An analysis of pediatric patients treated with Exjade in pooled clinical trials (n = 158) found a higher rate of renal adverse reactions among patients receiving doses greater than 25 mg/kg/day while their serum ferritin values were less than 1,000 mcg/L. Consider dose reduction or closer monitoring of renal and hepatic function, and serum ferritin levels during these periods. Use the minimum effective dose to maintain a low-iron burden [see Adverse Reactions (6.1), Use in Specific Populations (8.4)].

If the serum ferritin falls below 1,000 mcg/L at 2 consecutive visits, consider dose reduction, especially if the dose is greater than 25 mg/kg/day [see Adverse Reactions (6.1)]. If the serum ferritin falls below 500 mcg/L, interrupt therapy with Exjade and continue monthly monitoring. Evaluate the need for ongoing chelation for patients whose conditions do not require regular blood transfusions. Use the minimum effective dose to maintain iron burden in the target range. Continued administration of Exjade in the 20-40 mg/kg/day range when the body iron burden is approaching or within the normal range has resulted in life-threatening adverse reactions [see Dosage and Administration (2.1)].

For patients with NTDT, measure LIC by liver biopsy or by using an FDA-cleared or approved method for monitoring patients receiving deferasirox therapy every 6 months on treatment. Interrupt Exjade administration when the LIC is less than 3 mg Fe/g dw. Measure serum ferritin monthly, and if the serum ferritin falls below 300 mcg/L, interrupt Exjade and obtain a confirmatory LIC [see Clinical Studies (14)].

5.7 Hypersensitivity

Exjade may cause serious hypersensitivity reactions (such as anaphylaxis and angioedema), with the onset of the reaction usually occurring within the first month of treatment [see Adverse Reactions (6.2)]. If reactions are severe, discontinue Exjade and institute appropriate medical intervention. Exjade is contraindicated in patients with known hypersensitivity to deferasirox products and should not be reintroduced in patients who have experienced previous hypersensitivity reactions on deferasirox products due to the risk of anaphylactic shock.

5.8 Severe Skin Reactions

Severe cutaneous adverse reactions (SCARs) including Stevens-Johnson syndrome (SJS), toxic epidermal necrolysis (TEN), and drug reaction with eosinophilia and systemic symptoms (DRESS), which could be life-threatening or fatal have been reported during Exjade therapy [see Adverse Reactions (6.1, 6.2)]. Cases of erythema multiforme have been observed. Advise patients of the signs and symptoms of severe skin reactions, and closely monitor. If any severe skin reactions are suspected, discontinue Exjade immediately and do not reintroduce Exjade therapy.

5.9 Skin Rash

Rashes may occur during Exjade treatment [see Adverse Reactions (6.1)]. For rashes of mild to moderate severity, Exjade may be continued without dose adjustment, since the rash often resolves spontaneously. In severe cases, interrupt treatment with Exjade. Reintroduction at a lower dose with escalation may be considered after resolution of the rash.

5.10 Auditory and Ocular Abnormalities

Auditory disturbances (high frequency hearing loss, decreased hearing), and ocular disturbances (lens opacities, cataracts, elevations in intraocular pressure, and retinal disorders) were reported at a frequency of less than 1% with Exjade therapy in the clinical studies. The frequency of auditory adverse reactions was increased among pediatric patients who received Exjade doses greater than 25 mg/kg/day when serum ferritin was less than 1,000 mcg/L [see Warnings and Precautions (5.6)].

Perform auditory and ophthalmic testing (including slit-lamp examinations and dilated fundoscopy) before starting Exjade treatment and thereafter at regular intervals (every 12 months). If disturbances are noted, monitor more frequently. Consider dose reduction or interruption.

6 ADVERSE REACTIONS

The following clinically significant adverse reactions are also discussed in other sections of the labeling:

- Acute Kidney Injury, Including Acute Renal Failure Requiring Dialysis, and Renal Tubular Toxicity Including Fanconi Syndrome [see Warnings and Precautions (5.1, 5.6)]
- Hepatic Toxicity and Failure [see Warnings and Precautions (5.2, 5.6)]
- GI Hemorrhage [see Warnings and Precautions (5.3)]
- Bone Marrow Suppression [see Warnings and Precautions (5.4)]
- Hypersensitivity [see Warnings and Precautions (5.7)]
- Severe Skin Reactions [see Warnings and Precautions (5.8)]
- Skin Rash [see Warnings and Precautions (5.9)]
- Auditory and Ocular Abnormalities [see Warnings and Precautions (5.10)]

6.1 Clinical Trials Experience

Because clinical trials are conducted under widely varying conditions, adverse reaction rates observed in the clinical trials of a drug cannot be directly compared to rates in the clinical trials of another drug and may not reflect the rates observed in practice.

Transfusional Iron Overload

A total of 700 adult and pediatric patients were treated with Exjade (deferasirox) for 48 weeks in premarketing studies. These included 469 patients with beta-thalassemia, 99 with rare anemias, and 132 with sickle cell disease. Of these patients, 45% were male, 70% were Caucasian, and 292 patients were less than 16 years of age. In the sickle cell disease population, 89% of patients were black. Median treatment duration among the sickle cell patients was 51 weeks. Of the 700 patients treated, 469 (403 beta-thalassemia and 66 rare anemias) were entered into extensions of the original clinical protocols. In ongoing extension studies, median durations of treatment were 88-205 weeks.

Six hundred twenty-seven (627) patients with myelodysplastic syndrome (MDS) were enrolled across 5 uncontrolled trials. These studies varied in duration from 1 to 5 years. The discontinuation rate across studies in the first year was 46% (adverse events 20%, withdrawal of consent 10%, death 8%, other 4%, lab abnormalities 3%, and lack of efficacy 1%). Among 47 patients enrolled in the study of 5-year duration, 10 remained on Exjade at the completion of the study.

Table 1 displays adverse reactions occurring in greater than 5% of Exjade-treated beta-thalassemia patients (Study 1), sickle cell disease patients (Study 3), and patients with MDS (MDS pool). Abdominal pain, nausea, vomiting, diarrhea, skin rashes, and increases in serum creatinine were the most frequent adverse reactions reported with a suspected relationship to Exjade. Gastrointestinal symptoms, increases in serum creatinine, and skin rash were dose related.

Table 1. Adverse Reactionsa Occurring in Greater Than 5% of Exjade-treated Patients in Study 1, Study 3, and MDS Pool
 | Study 1 (Beta-thalassemia) |  | Study 3 (Sickle Cell Disease) |  | MDS Pool
Adverse Reactions | Exjade N = 296 n (%) | Deferoxamine N = 290 n (%) | Exjade N = 132 n (%) | Deferoxamine N = 63 n (%) | Exjade N = 627 n (%)
Abdominal Painb | 63 (21) | 41 (14) | 37 (28) | 9 (14) | 145 (23)
Diarrhea | 35 (12) | 21 (7) | 26 (20) | 3 (5) | 297 (47)
Creatinine Increasedc | 33 (11) | 0 (0) | 9 (7) | 0 | 89 (14)
Nausea | 31 (11) | 14 (5) | 30 (23) | 7 (11) | 161 (26)
Vomiting | 30 (10) | 28 (10) | 28 (21) | 10 (16) | 83 (13)
Rash | 25 (8) | 9 (3) | 14 (11) | 3 (5) | 83 (13)
Abbreviation: MDS, myelodysplastic syndrome.
aAdverse reaction frequencies are based on adverse events reported regardless of relationship to study drug.
bIncludes ‘abdominal pain’, ‘abdominal pain lower’, and ‘abdominal pain upper’.
cIncludes ‘blood creatinine increased’ and ‘blood creatinine abnormal’. See also Table 2.

In Study 1, a total of 113 (38%) patients treated with Exjade had increases in serum creatinine greater than 33% above baseline on 2 separate occasions (Table 2) and 25 (8%) patients required dose reductions. Increases in serum creatinine appeared to be dose related [see Warnings and Precautions (5.1)]. In this study, 17 (6%) patients treated with Exjade developed elevations in serum glutamic-pyruvic transaminase (SGPT)/ALT levels greater than 5 times the upper limit of normal (ULN) at 2 consecutive visits. Of these, 2 patients had liver biopsy proven drug-induced hepatitis and both discontinued Exjade therapy [see Warnings and Precautions (5.2)]. An additional 2 patients, who did not have elevations in SGPT/ALT greater than 5 times the ULN, discontinued Exjade because of increased SGPT/ALT. Increases in transaminases did not appear to be dose related. Adverse reactions that led to discontinuations included abnormal liver function tests (2 patients) and drug-induced hepatitis (2 patients), skin rash, glycosuria/proteinuria, Henoch Schönlein purpura, hyperactivity/insomnia, drug fever, and cataract (1 patient each).

In Study 3, a total of 48 (36%) patients treated with Exjade had increases in serum creatinine greater than 33% above baseline on 2 separate occasions (Table 2) [see Warnings and Precautions (5.1)]. Of the patients who experienced creatinine increases in Study 3, 8 Exjade-treated patients required dose reductions. In this study, 5 patients in the Exjade group developed elevations in SGPT/ALT levels greater than 5 times the ULN at 2 consecutive visits and 1 patient subsequently had Exjade permanently discontinued. Four additional patients discontinued Exjade due to adverse reactions with a suspected relationship to study drug, including diarrhea, pancreatitis associated with gallstones, atypical tuberculosis, and skin rash.

In the MDS pool, in the first year, a total of 229 (37%) patients treated with Exjade had increases in serum creatinine greater than 33% above baseline on 2 consecutive occasions (Table 2) and 8 (3.5%) patients permanently discontinued [see Warnings and Precautions (5.1)]. A total of 5 (0.8%) patients developed SGPT/ALT levels greater than 5 times the ULN at 2 consecutive visits. The most frequent adverse reactions that led to discontinuation included increases in serum creatinine, diarrhea, nausea, rash, and vomiting. Death was reported in the first year in 52 (8%) of patients [see Clinical Studies (14)].

Table 2. Number (%) of Patients with Increases in Serum Creatinine or SGPT/ALT in Study 1, Study 3, and MDS Pool
 | Study 1 (Beta-thalassemia) |  | Study 3 (Sickle Cell Disease) |  | MDS Pool
Laboratory Parameter | Exjade N = 296 n (%) | Deferoxamine N = 290 n (%) | Exjade N = 132 n (%) | Deferoxamine N = 63 n (%) | Exjade N = 627 n (%)
Serum Creatinine
Creatinine increase > 33% at 2 consecutive post-baseline visits | 113 (38) | 41 (14) | 48 (36) | 14 (22) | 229 (37)
Creatinine increase > 33% and > ULN at 2 consecutive post-baseline visits | 7 (2) | 1 (0) | 3 (2) | 2 (3) | 126 (20)
SGPT/ALT
SGPT/ALT > 5 x ULN at 2 post-baseline visits | 25 (8) | 7 (2) | 2 (2) | 0 | 9 (1)
SGPT/ALT > 5 x ULN at 2 consecutive post-baseline visits | 17 (6) | 5 (2) | 5 (4) | 0 | 5 (1)
Abbreviations: ALT, alanine transaminase; MDS, myelodysplastic syndrome; SGPT, serum glutamic-pyruvic transaminase; ULN, upper limit of normal.

Non-Transfusion-Dependent Thalassemia Syndromes

In Study 5, 110 patients with NTDT received 1 year of treatment with Exjade 5 or 10 mg/kg/day and 56 patients received placebo in a double-blind, randomized trial. In Study 6, 130 of the patients who completed Study 5 were treated with open-label Exjade at 5, 10, or 20 mg/kg/day (depending on the baseline LIC) for 1 year [see Clinical Studies (14)]. In Study 7, 134 patients with NTDT of 10 years of age or older with iron overload, received Exjade for up to 5 years, at a starting dose of 10 mg/kg/day followed by dose adjustment at Week 4, and then approximately every 6 months thereafter based on LIC levels. Tables 3 and 4 display the frequency of adverse reactions in patients with NTDT. Adverse reactions with a suspected relationship to study drug were included in Table 3 if they occurred at ≥ 5% of patients in Study 5.

Table 3. Adverse Reactions Occurring in Greater Than 5% in Patients with NTDT
 | Study 5 |  | Study 6 | Study 7
 | Exjade | Placebo | Exjade | Exjade
 | N = 110 | N = 56 | N = 130 | N = 134
 | n (%) | n (%) | n (%) | n (%)
Any adverse reaction | 31 (28) | 9 (16) | 27 (21) | 50 (37)
Nausea | 7 (6) | 4 (7) | 2 (2)a | 7 (5)
Rash | 7 (6) | 1 (2) | 2 (2)a | 3 (2)a
Diarrhea | 5 (5) | 1 (2) | 7 (5) | 8 (6)
Abbreviation: NTDT, non-transfusion-dependent thalassemia.
a The occurrence of nausea, and rash are included for Study 6 and rash for Study 7 for consistency. There were no additional adverse reactions with a suspected relationship to study drug occurring in greater than 5% of patients in Study 6 and Study 7.

In Study 5, 1 patient in the placebo 10 mg/kg/day group experienced an ALT increase to greater than 5 times ULN and greater than 2 times baseline (Table 4). Three Exjade-treated patients (all in the 10 mg/kg/day group) had 2 consecutive serum creatinine level increases greater than 33% from baseline and greater than ULN. Serum creatinine returned to normal in all 3 patients (in 1 spontaneously and in the other 2 after drug interruption). Two additional cases of ALT increase and 2 additional cases of serum creatinine increase were observed in the 1-year extension of Study 5. The number (%) of patients with NTDT with increase in serum creatinine or SGPT/ALT in Study 5, Study 6, and Study 7 are presented in Table 4 below.

Table 4. Number (%) of Patients with NTDT with Increases in Serum Creatinine or SGPT/ALT
 | Study 5 |  | Study 6 | Study 7
 | Exjade | Placebo | Exjade | Exjade
 | N = 110 | N = 56 | N = 130 | N = 134
Laboratory Parameter | n (%) | n (%) | n (%) | n (%)
Serum creatinine (> 33% increase from baseline and > ULN at ≥ 2 consecutive post-baseline values) | 3 (3) | 0 | 2 (2) | 2 (2)
SGPT/ALT (> 5 x ULN and > 2 x baseline) | 1 (1) | 1 (2) | 2 (2) | 1 (1)
Abbreviations: ALT, alanine transaminase; NTDT, non-transfusion-dependent thalassemia; SGPT, serum glutamic-pyruvic transaminase; ULN, upper limit of normal.

Proteinuria

In clinical studies, urine protein was measured monthly. Intermittent proteinuria (urine protein/creatinine ratio greater than 0.6 mg/mg) occurred in 18.6% of Exjade-treated patients compared to 7.2% of deferoxamine-treated patients in Study 1 [see Warnings and Precautions (5.1)].

Other Adverse Reactions

In the population of more than 5,000 patients with transfusional iron overload who have been treated with Exjade during clinical trials, adverse reactions occurring in 0.1% to 1% of patients included gastritis, edema, sleep disorder, pigmentation disorder, dizziness, anxiety, maculopathy, cholelithiasis, pyrexia, fatigue, laryngeal pain, cataract, hearing loss, GI hemorrhage, gastric ulcer (including multiple ulcers), duodenal ulcer, renal tubular disorder (Fanconi Syndrome), and acute pancreatitis (with and without underlying biliary conditions). Adverse reactions occurring in 0.01% to 0.1% of patients included optic neuritis, esophagitis, erythema multiforme, and drug reaction with eosinophilia and systemic symptoms (DRESS). Adverse reactions, which most frequently led to dose interruption or dose adjustment during clinical trials were rash, GI disorders, infections, increased serum creatinine, and increased serum transaminases.

Pooled Analysis of Pediatric Clinical Trial Data

A nested case control analysis was conducted within a deferasirox tablets for oral suspension pediatric pooled clinical trial dataset to evaluate the effects of dose and serum ferritin level, separately and combined, on kidney function. Among 1213 children (aged 2 to 15 years) with transfusion-dependent thalassemia, 162 cases of acute kidney injury (eGFR < 90 mL/min/1.73 m^2) and 621 matched-controls with normal kidney function (eGFR > 120 mL/min/1.73 m^2) were identified. The primary findings were:

- A 26% increased risk of acute kidney injury was observed with each 5 mg/kg increase in daily Exjade dosage starting at 20 mg/kg/day (95% confidence interval (CI): 1.08-1.48).

- A 25% increased risk for acute kidney injury was observed with each 250 mcg/L decrease in serum ferritin starting at 1250 mcg/L (95% CI: 1.01-1.56).

- Among pediatric patients with a serum ferritin < 1,000 mcg/L, those who received Exjade dosage > 30 mg/kg/day, compared to those who received lower dosages, had a higher risk for acute kidney injury (Odds ratio (OR) = 4.47, 95% CI: 1.25-15.95), consistent with overchelation.

In addition, a cohort based analysis of ARs was conducted in the deferasirox tablets for oral suspension pediatric pooled clinical trial data. Pediatric patients who received Exjade dose > 25 mg/kg/day when their serum ferritin was < 1,000 mcg/L (n = 158) had a 6-fold greater rate of renal adverse reactions (incidence rate ration (IRR) = 6.00, 95% CI: 1.75-21.36) and a 2-fold greater rate of dose interruptions (IRR = 2.06, 95% CI: 1.33-3.17) compared to the time-period prior to meeting these simultaneous criteria. Adverse reaction of special interest (cytopenia, renal, hearing, and GI disorders) occurred 1.9-fold more frequently when these simultaneous criteria were met, compared to preceding time-periods (IRR = 1.91, 95% CI: 1.05-3.48) [see Warnings and Precautions (5.6)].

6.2 Postmarketing Experience

The following adverse reactions have been spontaneously reported during postapproval use of Exjade in the transfusional-iron overload setting. Because these reactions are reported voluntarily from a population of uncertain size, in which patients may have received concomitant medication, it is not always possible to reliably estimate frequency or establish a causal relationship to drug exposure.

Skin and Subcutaneous Tissue Disorders: Stevens-Johnson syndrome (SJS), hypersensitivity vasculitis, urticaria, alopecia, toxic epidermal necrolysis (TEN)

Immune System Disorders: hypersensitivity reactions (including anaphylactic reaction and angioedema)

Renal and Urinary Disorders: acute renal failure, tubulointerstitial nephritis

Hepatobiliary Disorders: hepatic failure

Gastrointestinal Disorders: GI perforation

Blood and Lymphatic System Disorders: worsening anemia

5-Year Pediatric Registry

In a 5-year observational study, 267 pediatric patients 2 to < 6 years of age (at enrollment) with transfusional hemosiderosis received deferasirox. Of the 242 patients who had pre- and post-baseline eGFR measurements, 116 (48%) patients had a decrease in eGFR of ≥ 33% observed at least once. Twenty-one (18%) of these 116 patients with decreased eGFR had a dose interruption, and 15 (13%) of these 116 patients had a dose decrease within 30 days. Adverse reactions leading to permanent discontinuation from the study included liver injury (n = 11), renal tubular disorder
(n = 1), proteinuria (n = 1), hematuria (n = 1), upper GI hemorrhage (n = 1), vomiting (n = 2), abdominal pain (n = 1), and hypokalemia (n = 1).

7 DRUG INTERACTIONS

7.1 Aluminum-Containing Antacid Preparations

The concomitant administration of Exjade and aluminum-containing antacid preparations has not been formally studied. Although deferasirox has a lower affinity for aluminum than for iron, do not take Exjade with aluminum-containing antacid preparations due to the mechanism of action of Exjade.

7.2 Agents Metabolized by CYP3A4

Deferasirox may induce CYP3A4 resulting in a decrease in CYP3A4 substrate concentration when these drugs are coadministered. Closely monitor patients for signs of reduced effectiveness when deferasirox is administered with drugs metabolized by CYP3A4 (e.g., alfentanil, aprepitant, budesonide, buspirone, conivaptan, cyclosporine, darifenacin, darunavir, dasatinib, dihydroergotamine, dronedarone, eletriptan, eplerenone, ergotamine, everolimus, felodipine, fentanyl, hormonal contraceptive agents, indinavir, fluticasone, lopinavir, lovastatin, lurasidone, maraviroc, midazolam, nisoldipine, pimozide, quetiapine, quinidine, saquinavir, sildenafil, simvastatin, sirolimus, tacrolimus, tolvaptan, tipranavir, triazolam, ticagrelor, and vardenafil) [see Clinical Pharmacology (12.3)].

7.3 Agents Metabolized by CYP2C8

Deferasirox inhibits CYP2C8 resulting in an increase in CYP2C8 substrate (e.g., repaglinide and paclitaxel) concentration when these drugs are coadministered. If Exjade and repaglinide are used concomitantly, consider decreasing the dose of repaglinide and perform careful monitoring of blood glucose levels. Closely monitor patients for signs of exposure related toxicity when Exjade is coadministered with other CYP2C8 substrates [see Clinical Pharmacology (12.3)].

7.4 Agents Metabolized by CYP1A2

Deferasirox inhibits CYP1A2 resulting in an increase in CYP1A2 substrate (e.g., alosetron, caffeine, duloxetine, melatonin, ramelteon, tacrine, theophylline, tizanidine) concentration when these drugs are coadministered. An increase in theophylline plasma concentrations could lead to clinically significant theophylline-induced CNS or other adverse reactions. Avoid the concomitant use of theophylline or other CYP1A2 substrates with a narrow therapeutic index (e.g., tizanidine) with Exjade. Monitor theophylline concentrations and consider theophylline dose modification if you must coadminister theophylline with Exjade. Closely monitor patients for signs of exposure related toxicity when Exjade is coadministered with other drugs metabolized by CYP1A2 [see Clinical Pharmacology (12.3)].

7.5 Agents Inducing UDP-glucuronosyltransferase (UGT) Metabolism

Deferasirox is a substrate of UGT1A1 and to a lesser extent UGT1A3. The concomitant use of Exjade with potent UGT inducers (e.g., rifampicin, phenytoin, phenobarbital, ritonavir) may result in a decrease in Exjade efficacy due to a possible decrease in deferasirox concentration. Avoid the concomitant use of potent UGT inducers with Exjade. Consider increasing the initial dose of Exjade if you must coadminister these agents together [see Dosage and Administration (2.5), Clinical Pharmacology (12.3)].

7.6 Bile Acid Sequestrants

Avoid the concomitant use of bile acid sequestrants (e.g., cholestyramine, colesevelam, colestipol) with Exjade due to a possible decrease in deferasirox concentration. If you must coadminister these agents together, consider increasing the initial dose of Exjade [see Dosage and Administration (2.5), Clinical Pharmacology (12.3)].

7.7 Busulfan

Increased exposure of busulfan was observed with concomitant use with deferasirox. Monitor plasma concentrations of busulfan when coadministered with deferasirox to allow dose adjustment of busulfan as needed [see Clinical Pharmacology (12.3)].

8 USE IN SPECIFIC POPULATIONS

8.1 Pregnancy

Risk Summary

There are no studies with the use of Exjade in pregnant women to inform drug-associated risks.

Administration of deferasirox to rats during pregnancy resulted in decreased offspring viability and an increase in renal anomalies in male offspring at doses that were about or less than the recommended human dose on an mg/m^2 basis. No fetal effects were noted in pregnant rabbits at doses equivalent to the human recommended dose on an mg/m^2 basis. Exjade should be used during pregnancy only if the potential benefit justifies the potential risk to the fetus.

The background risk of major birth defects and miscarriage for the indicated population is unknown. All pregnancies have a background risk of birth defect, loss, or other adverse outcomes. However, the background risk in the U.S. general population of major birth defects is 2% to 4% and of miscarriage is 15% to 20% of clinically recognized pregnancies.

Data

Animal Data

In embryo-fetal developmental studies, pregnant rats and rabbits received oral deferasirox during the period of organogenesis at doses up to 100 mg/kg/day in rats and 50 mg/kg/day in rabbits (1.2 times the maximum recommended human dose (MRHD) on an mg/m^2 basis). These doses resulted in maternal toxicity but no fetal harm was observed.

In a prenatal and postnatal developmental study, pregnant rats received oral deferasirox daily from organogenesis through lactation day 20 at doses of 10, 30, and 90 mg/kg/day (0.1, 0.3, and 1.0 times the MRHD on an mg/m^2 basis). Maternal toxicity, loss of litters, and decreased offspring viability occurred at 90 mg/kg/day (1.0 times the MRHD on a mg/m^2 basis) and increases in renal anomalies in male offspring occurred at 30 mg/kg/day (0.3 times the MRHD on a mg/m^2 basis).

8.2 Lactation

Risk Summary

No data are available regarding the presence of Exjade or its metabolites in human milk, the effects of the drug on the breastfed child, or the effects of the drug on milk production. Deferasirox and its metabolites were excreted in rat milk. Because many drugs are excreted in human milk, and because of the potential for serious adverse reactions in a breastfeeding child from deferasirox and its metabolites, a decision should be made whether to discontinue breastfeeding or to discontinue the drug, taking into account the importance of the drug to the mother.

8.3 Females and Males of Reproductive Potential

Contraception

Counsel patients to use non-hormonal method(s) of contraception since Exjade can render hormonal contraceptives ineffective [see Drug Interactions (7.2)].

8.4 Pediatric Use

Transfusional Iron Overload

The safety and effectiveness of Exjade have been established in pediatric patients 2 years of age and older for the treatment of transfusional iron overload [see Dosage and Administration (2.1)].

Safety and effectiveness have not been established in pediatric patients less than 2 years of age for the treatment of transfusional iron overload.

Pediatric approval for treatment of transfusional iron overload was based on clinical studies of 292 pediatric patients 2 years to less than 16 years of age with various congenital and acquired anemias. Seventy percent of these patients had beta-thalassemia [see Indications and Usage (1), Dosage and Administration (2.1), Clinical Studies (14)]. In those clinical studies, 173 children (ages 2 to < 12 years) and 119 adolescents (ages 12 to < 17 years) were exposed to deferasirox.

A trial conducted in treatment-naïve pediatric patients, 2 to < 18 years of age with transfusional iron overload (NCT02435212) did not provide additional relevant information about the safety or effectiveness of the deferasirox granules dosage form (Jadenu Sprinkle) compared to the deferasirox oral tablets for suspension dosage form (Exjade).

Iron Overload in Non-Transfusion-Dependent Thalassemia Syndromes

The safety and effectiveness of Exjade have been established in patients 10 years of age and older for the treatment of chronic iron overload with non-transfusion-dependent thalassemia (NTDT) syndromes [see Dosage and Administration (2.2)].

Safety and effectiveness have not been established in patients less than 10 years of age with chronic iron overload in NTDT syndromes.

Pediatric approval for treatment of NTDT syndromes with liver iron (Fe) concentration (LIC) of at least 5 mg Fe per gram of dry weight and a serum ferritin greater than 300 mcg/L was based on 16 pediatric patients treated with Exjade therapy (10 years to less than 16 years of age) with chronic iron overload and NTDT. Use of Exjade in these age groups is supported by evidence from adequate and well-controlled studies of Exjade in adult and pediatric patients [see Indications and Usage (1.2), Dosage and Administration (2.2), Clinical Studies (14)].

In general, risk factors for deferasirox-associated kidney injury include preexisting renal disease, volume depletion, overchelation, and concomitant use of other nephrotoxic drugs. Acute kidney injury, and acute liver injury and failure has occurred in pediatric patients. In a pooled safety analysis, pediatric patients with higher Exjade exposures had a greater probability of renal toxicity and decreased renal function, resulting in increased deferasirox exposure and progressive renal toxicity/kidney injury. Higher rates of renal adverse reactions have been identified among pediatric patients receiving Exjade doses greater than 25 mg/kg/day when their serum ferritin values were less than 1,000 mcg/L [see Dosage and Administration (2.5), Warnings and Precautions (5.1, 5.6), Adverse Reactions (6.1, 6.2)].

Monitoring Recommendations for pediatric patients with Transfusional Iron Overload and NTDT

It is recommended that serum ferritin be monitored every month to assess the patient’s response to therapy and to minimize the risk of overchelation [see Warnings and Precautions (5.6)].

Monitor renal function by estimating GFR using an eGFR prediction equation appropriate for pediatric patients and evaluate renal tubular function. Monitor renal function more frequently in pediatric patients in the presence of renal toxicity risk factors, including episodes of dehydration, fever and acute illness that may result in volume depletion or decreased renal perfusion. Use the minimum effective dose [see Warnings and Precautions (5.1)].

Interrupt Exjade in pediatric patients with transfusional iron overload and consider dose interruption in pediatric patients with non-transfusion-dependent iron overload, for acute illnesses, which can cause volume depletion, such as vomiting, diarrhea, or prolonged decreased oral intake, and monitor more frequently. Resume therapy as appropriate, based on assessments of renal function, when oral intake and volume status are normal. Evaluate the risk benefit profile of continued Exjade use in the setting of decreased renal function. Avoid use of other nephrotoxic drugs [see Dosage and Administration (2.5), Warnings and Precautions (5.1)].

Juvenile Animal Toxicity Data

Renal toxicity was observed in adult mice, rats, and marmoset monkeys administered deferasirox at therapeutic doses. In a neonatal and juvenile toxicity study in rats, deferasirox was administered orally from postpartum Day 7 through 70, which equates to a human age range of term neonate through adolescence. Increased renal toxicity was identified in juvenile rats compared to adult rats at a dose based on mg/m^2 approximately 0.4 times the recommended dose of 20 mg/kg/day. A higher frequency of renal abnormalities was noted when deferasirox was administered to non-iron overloaded animals compared to iron overloaded animals.

8.5 Geriatric Use

Four hundred thirty-one (431) patients greater than or equal to 65 years of age were studied in clinical trials of Exjade in the transfusional iron overload setting. Two hundred twenty-five (225) of these patients were between 65 and 75 years of age while 206 were greater than or equal to 75 years of age. The majority of these patients had myelodysplastic syndrome (MDS) (n = 393). In these trials, elderly patients experienced a higher frequency of adverse reactions than younger patients. Monitor elderly patients for early signs or symptoms of adverse reactions that may require a dose adjustment. Elderly patients are at increased risk for toxicity due to the greater frequency of decreased hepatic, renal, or cardiac function, and of concomitant disease or other drug therapy. Dose selection for an elderly patient should be cautious, usually starting at the low end of the dosing range.

In elderly patients, including those with MDS, individualize the decision to remove accumulated iron based on clinical circumstances and the anticipated clinical benefit and risks of Exjade therapy.

8.6 Renal Impairment

Exjade is contraindicated in patients with eGFR less than 40 mL/min/1.73 m^2 [see Contraindications (4)]. For patients with renal impairment (eGFR 40–60 mL/min/1.73 m^2), reduce the starting dose by 50% [see Dosage and Administration (2.4)]. Exercise caution in pediatric patients with eGFR between 40 and 60 mL/min/1.73 m^2 [see Dosage and Administration (2.4)]. If treatment is needed, use the minimum effective dose with enhanced monitoring of glomerular and renal tubular function. Individualize dose titration based on improvement in renal injury [see Dosage and Administration (2.4, 2.5)].

Exjade can cause glomerular dysfunction, renal tubular toxicity, or both, and can result in acute renal failure. Monitor all patients closely for changes in eGFR and renal tubular dysfunction during Exjade treatment. If either develops, consider dose reduction, interruption or discontinuation of Exjade until glomerular or renal tubular function returns to baseline [see Dosage and Administration (2.4, 2.5), Warnings and Precautions (5.1)].

8.7 Hepatic Impairment

Avoid the use of Exjade in patients with severe (Child-Pugh C) hepatic impairment. For patients with moderate (Child-Pugh B) hepatic impairment, the starting dose should be reduced by 50%. Closely monitor patients with mild (Child-Pugh A) or moderate (Child-Pugh B) hepatic impairment for efficacy and adverse reactions that may require dose titration [see Dosage and Administration (2.4), Warnings and Precautions (5.2)].

10 OVERDOSAGE

Cases of overdose (2-3 times the prescribed dose for several weeks) have been reported. In one case, this resulted in hepatitis, which resolved without long-term consequences after a dose interruption. In one pediatric case, a dose of 2-3 times the prescribed dose for 6 days, resulted in acute renal failure requiring hemofiltration and acute liver injury/failure, which were reversible with intensive care support. Single doses up to 80 mg per kg per day in iron overloaded beta-thalassemic patients have been tolerated with nausea and diarrhea noted. In healthy volunteers, single doses of up to 40 mg per kg per day were tolerated.

Early signs of acute overdose are digestive effects such as abdominal pain, diarrhea, nausea, and vomiting. Hepatic and renal disorders have been reported, including cases of liver enzyme and creatinine increased with recovery after treatment discontinuation. An erroneously administered single dose of 90 mg/kg led to Fanconi syndrome which resolved after treatment.

There is no specific antidote for Exjade. In case of overdose, it may be treated with induction of vomiting or gastric lavage, and by symptomatic treatment.

11 DESCRIPTION

Exjade (deferasirox) is an iron chelating agent. Exjade tablets for oral suspension contain 125 mg, 250 mg, or 500 mg deferasirox. Deferasirox is designated chemically as 4-[3,5-Bis (2-hydroxyphenyl)-1H-1,2,4-triazol-1-yl]-benzoic acid and its structural formula is:

Deferasirox is a white to slightly yellow powder. Its molecular formula is C21H15N3O4 and its molecular weight is 373.4 g/mol.

Inactive Ingredients: Crospovidone (NF), lactose monohydrate (NF), magnesium stearate (NF), microcrystalline cellulose (NF), povidone (K30) (NF), silicon dioxide (NF), and sodium lauryl sulphate (NF).

12 CLINICAL PHARMACOLOGY

12.1 Mechanism of Action

Exjade (deferasirox) is an orally active chelator that is selective for iron (as Fe^3+). It is a tridentate ligand that binds iron with high affinity in a 2:1 ratio. Although deferasirox has very low affinity for zinc and copper there are variable decreases in the serum concentration of these trace metals after the administration of deferasirox. The clinical significance of these decreases is uncertain.

12.2 Pharmacodynamics

Pharmacodynamic effects tested in an iron balance metabolic study showed that deferasirox (10, 20, and 40 mg per kg per day) was able to induce a mean net iron excretion (0.119, 0.329, and 0.445 mg Fe/kg body weight per day, respectively) within the clinically relevant range (0.1-0.5 mg per kg per day). Iron excretion was predominantly fecal.

An analysis of pooled pediatric clinical trial data found a statistically significant relationship between exposure and the probability of renal toxicity (increase in serum creatinine and urinary protein), resulting in a decrease in renal function. Decreases in renal function resulted in an increase in deferasirox exposure, which may increase the probability of renal toxicity.

Cardiac Electrophysiology

At the maximum approved recommended dose, deferasirox does not prolong the QT interval to any clinically relevant extent.

12.3 Pharmacokinetics

Absorption

Exjade is absorbed following oral administration with median times to maximum plasma concentration (Tmax) of about 1.5-4 hours. The Cmax and area under the curve (AUC) of deferasirox increase approximately linearly with dose after both single administration and under steady-state conditions. Exposure to deferasirox increased by an accumulation factor of 1.3-2.3 after multiple doses. The absolute bioavailability (AUC) of deferasirox tablets for oral suspension is 70% compared to an intravenous dose. The bioavailability (AUC) of deferasirox was variably increased when taken with a meal.

Distribution

Deferasirox is highly (~99%) protein bound almost exclusively to serum albumin. The percentage of deferasirox confined to the blood cells was 5% in humans. The volume of distribution at steady state (Vss) of deferasirox is 14.37 ± 2.69 L in adults.

Metabolism

Glucuronidation is the main metabolic pathway for deferasirox, with subsequent biliary excretion. Deconjugation of glucuronidates in the intestine and subsequent reabsorption (enterohepatic recycling) is likely to occur. Deferasirox is mainly glucuronidated by UGT1A1 and to a lesser extent UGT1A3. CYP450-catalyzed (oxidative) metabolism of deferasirox appears to be minor in humans (about 8%). Deconjugation of glucuronide metabolites in the intestine and subsequent reabsorption (enterohepatic recycling) was confirmed in a healthy volunteer study in which the administration of cholestyramine 12 g twice daily (strongly binds to deferasirox and its conjugates) 4 and 10 hours after a single dose of deferasirox resulted in a 45% decrease in deferasirox exposure (AUC) by interfering with the enterohepatic recycling of deferasirox.

Excretion

Deferasirox and metabolites are primarily (84% of the dose) excreted in the feces. Renal excretion of deferasirox and metabolites is minimal (8% of the administered dose). The mean elimination half-life (t1/2) ranged from 8-16 hours following oral administration.

Drug Interactions

Midazolam: In healthy volunteers, the concomitant administration of Exjade and midazolam (a CYP3A4 probe substrate) resulted in a decrease of midazolam peak concentration by 23% and exposure by 17%. In the clinical setting, this effect may be more pronounced. The study was not adequately designed to conclusively assess the potential induction of CYP3A4 by deferasirox [see Drug Interactions (7.2)].

Repaglinide: In a healthy volunteer study, the concomitant administration of Exjade (30 mg per kg/day for 4 days) and the CYP2C8 probe substrate repaglinide (single dose of 0.5 mg) resulted in an increase in repaglinide systemic exposure (AUC) to 2.3-fold of control and an increase in Cmax of 62% [see Drug Interactions (7.3)].

Theophylline: In a healthy volunteer study, the concomitant administration of Exjade (repeated dose of 30 mg per kg/day) and the CYP1A2 substrate theophylline (single dose of 120 mg) resulted in an approximate doubling of the theophylline AUC and elimination half-life. The single dose Cmax was not affected, but an increase in theophylline Cmax is expected to occur with chronic dosing [see Drug Interactions (7.4)].

Rifampicin: In a healthy volunteer study, the concomitant administration of Exjade (single dose of 30 mg per kg) and the potent UDP-glucuronosyltransferase (UGT) inducer rifampicin (600 mg/day for 9 days) resulted in a decrease of deferasirox systemic exposure (AUC) by 44% [see Drug Interactions (7.5)].

Cholestyramine: The concomitant use of Exjade with bile acid sequestrants may result in a decrease in Exjade efficacy. In healthy volunteers, the administration of cholestyramine after a single dose of deferasirox resulted in a 45% decrease in deferasirox exposure (AUC) [see Drug Interactions (7.6)].

Busulfan: Concomitant administration of deferasirox and busulfan resulted in an increase of busulfan exposure (AUC).

In vitro Studies:

- Cytochrome P450 Enzymes: Deferasirox inhibits human CYP3A4, CYP2C8, CYP1A2, CYP2A6, CYP2D6, and CYP2C19 in vitro.
- Transporter Systems: The addition of cyclosporin A (PgP/MRP1/MRP2 inhibitor) or verapamil (PgP/MRP1 inhibitor) did not influence ICL670 permeability in vitro.

Pharmacokinetics in Specific Populations

Pediatric: Following oral administration of single or multiple doses, systemic exposure of adolescents and children to deferasirox was less than in adult patients. In children less than 6 years of age, systemic exposure was about 50% lower than in adults.

Geriatric: The pharmacokinetics of deferasirox have not been studied in elderly patients (65 years of age or older).

Gender: Females have a moderately lower apparent clearance (by 17.5%) for deferasirox compared to males.

Renal Impairment: Compared to patients with MDS and eGFR greater than 60 mL/min/1.73 m^2, patients with MDS and eGFR 40 to 60 mL/min/1.73 m^2 (n = 34) had approximately 50% higher mean deferasirox trough plasma concentrations.

Hepatic Impairment: In a single dose (20 mg/kg) study in patients with varying degrees of hepatic impairment, deferasirox exposure was increased compared to patients with normal hepatic function. The average total (free and bound) AUC of deferasirox increased 16% in 6 patients with mild (Child-Pugh A) hepatic impairment, and 76% in 6 patients with moderate (Child-Pugh B) hepatic impairment compared to 6 patients with normal hepatic function. The impact of severe (Child-Pugh C) hepatic impairment was assessed in only 1 patient.

13 NONCLINICAL TOXICOLOGY

13.1 Carcinogenesis, Mutagenesis, Impairment of Fertility

A 104-week oral carcinogenicity study in Wistar rats showed no evidence of carcinogenicity from deferasirox at doses up to 60 mg per kg per day (0.48 times the MRHD on an mg/m^2 basis). A 26-week oral carcinogenicity study in p53 (+/-) transgenic mice has shown no evidence of carcinogenicity from deferasirox at doses up to 200 mg per kg per day (0.81 times the MRHD on a mg/m^2 basis) in males and 300 mg per kg per day (1.21 times the MRHD on a mg/m^2 basis) in females.

Deferasirox was negative in the Ames test and chromosome aberration test with human peripheral blood lymphocytes. It was positive in 1 of 3 in vivo oral rat micronucleus tests.

Deferasirox at oral doses up to 75 mg per kg per day (0.6 times the MRHD on a mg/m^2 basis) was found to have no adverse effect on fertility and reproductive performance of male and female rats.

14 CLINICAL STUDIES

Transfusional Iron Overload

The primary efficacy study, Study 1 (NCT00061750), was a multicenter, open-label, randomized, active-comparator control study to compare Exjade (deferasirox) and deferoxamine in patients with beta-thalassemia and transfusional hemosiderosis. Patients greater than or equal to 2 years of age were randomized in a 1:1 ratio to receive either oral Exjade at starting doses of 5, 10, 20, or 30 mg per kg once daily or subcutaneous deferoxamine at starting doses of 20 to 60 mg per kg for at least 5 days per week based on LIC at baseline (2-3, greater than 3-7, greater than 7-14, and greater than 14 mg Fe/g dry weight). Patients randomized to deferoxamine who had LIC values less than 7 mg Fe/g dry weight were permitted to continue on their prior deferoxamine dose, even though the dose may have been higher than specified in the protocol.

Patients were to have a liver biopsy at baseline and end of study (after 12 months) for LIC. The primary efficacy endpoint was defined as a reduction in LIC of greater than or equal to 3 mg Fe/g dry weight for baseline values greater than or equal to 10 mg Fe/g dry weight, reduction of baseline values between 7 and less than 10 to less than 7 mg Fe/g dry weight, or maintenance or reduction for baseline values less than 7 mg Fe/g dry weight.

A total of 586 patients were randomized and treated, 296 with Exjade and 290 with deferoxamine. The mean age was 17.1 years (range, 2-53 years); 52% were females and 88% were Caucasian. The primary efficacy population consisted of 553 patients (Exjade n = 276; deferoxamine n = 277) who had LIC evaluated at baseline and 12 months or discontinued due to an adverse reaction. The percentage of patients achieving the primary endpoint was 52.9% for Exjade and 66.4% for deferoxamine. The relative efficacy of Exjade to deferoxamine cannot be determined from this study.

In patients who had an LIC at baseline and at end of study, the mean change in LIC was -2.4 mg Fe/g dry weight in patients treated with Exjade and -2.9 mg Fe/g dry weight in patients treated with deferoxamine.

Reduction of LIC and serum ferritin was observed with Exjade doses of 20 to 30 mg per kg per day. Exjade doses below 20 mg per kg per day failed to provide consistent lowering of LIC and serum ferritin levels (Figure 1). Therefore, a starting dose of 20 mg per kg per day is recommended [see Dosage and Administration (2.1)].

Figure 1. Changes in Liver Iron Concentration and Serum Ferritin Following Exjade (5-30 mg per kg per day) in Study 1

Study 2 (NCT00061763) was an open-label, noncomparative trial of efficacy and safety of Exjade given for 1 year to patients with chronic anemias and transfusional hemosiderosis. Similar to Study 1, patients received 5, 10, 20, or 30 mg per kg per day of Exjade based on baseline LIC.

A total of 184 patients were treated in this study: 85 patients with beta-thalassemia and 99 patients with other congenital or acquired anemias (myelodysplastic syndromes, n = 47; Diamond-Blackfan syndrome, n = 30; other, n = 22). Nineteen percent (19%) of patients were less than 16 years of age and 16% were greater than 65 years of age. There was a reduction in the absolute LIC from baseline to end of study (-4.2 mg Fe/g dry weight).

Study 3 (NCT00067080) was a multicenter, open-label, randomized trial of the safety and efficacy of Exjade relative to deferoxamine given for 1 year in patients with sickle cell disease and transfusional hemosiderosis. Patients were randomized to Exjade at doses of 5, 10, 20, or 30 mg per kg per day or subcutaneous deferoxamine at doses of 20-60 mg per kg per day for 5 days per week according to baseline LIC.

A total of 195 patients were treated in this study: 132 with Exjade and 63 with deferoxamine. Forty-four percent (44%) of patients were less than 16 years of age and 91% were black. At end of study, the mean change in LIC (as measured by magnetic susceptometry by a superconducting quantum interference device) in the per protocol-1 (PP-1) population, which consisted of patients who had at least 1 post-baseline LIC assessment, was -1.3 mg Fe/g dry weight for patients receiving Exjade (n = 113) and -0.7 mg Fe/g dry weight for patients receiving deferoxamine (n = 54).

One-hundred five (105) patients with thalassemia major and cardiac iron overload were enrolled in a study assessing the change in cardiac magnetic resonance imaging (MRI) T2* value (measured in milliseconds, ms) before and after treatment with deferasirox. Cardiac T2* values at baseline ranged from 5 to less than 20 ms. The geometric mean of cardiac T2* in the 68 patients who completed 3 years of Exjade therapy increased from 11.98 ms at baseline to 17.12 ms at 3 years. Cardiac T2* values improved in patients with severe cardiac iron overload (less than 10 ms) and in those with mild to moderate cardiac iron overload (greater than or equal to 10 to less than 20 ms). The clinical significance of these observations is unknown.

Six hundred twenty-seven (627) patients with MDS were enrolled across 5 uncontrolled trials. Two hundred thirty-nine (239) of the 627 patients were enrolled in trials that limited enrollment to patients with IPSS Low or Intermediate 1 risk MDS, and the remaining 388 patients were enrolled in trials that did not specify MDS risk stratification but required a life expectancy of greater than 1 year. Planned duration of treatment in these trials ranged from 1 year (365 patients) to 5 years (47 patients). These trials evaluated the effects of Exjade therapy on parameters of iron overload, including LIC (125 patients) and serum ferritin (627 patients). The percent of patients completing planned duration of treatment was 51% in the largest 1-year study, 52% in the 3-year study and 22% in the 5-year study. The major causes for treatment discontinuation were withdrawal of consent, adverse reaction, and death. Over 1 year of follow-up across these pooled studies, mean change in serum ferritin was -332.8 (± 2615.59) mcg/L (n = 593) and mean change in LIC was -5.9 (± 8.32) mg Fe/g dw (n = 68). Results of these pooled studies in 627 patients with MDS suggest a progressive decrease in serum ferritin and LIC beyond 1 year in those patients who are able to continue Exjade.

Study 4 (TELESTO; NCT00940602) was a randomized, double-blind, placebo-controlled trial performed in 225 patients with MDS (Low/Int-1 risk) and transfusional iron overload of which 149 were treated with deferasirox and 76 received placebo. The observed hazard ratio of 0.64 (95% CI: 0.42, 0.96) suggests a positive impact of deferasirox on event-free survival (EFS, a composite endpoint defined as death, worsening cardiac function, hospitalization for congestive heart failure, liver function impairment, liver cirrhosis, or progression to acute myeloid leukemia, whichever occurred first).

Non-Transfusion Dependent Thalassemia

Study 5 (NCT00873041) was a randomized, double-blind, placebo-controlled trial of treatment with Exjade for patients 10 years of age or older with NTDT syndromes and iron overload. Eligible patients had an LIC of at least 5 mg Fe/g dw measured by R2 MRI and a serum ferritin exceeding 300 mcg/L at screening (2 consecutive values at least 14 days apart from each other). A total of 166 patients were randomized, 55 to the Exjade 5 mg/kg/day dose group, 55 to the Exjade 10 mg/kg/day dose group, and 56 to placebo (28 to each matching placebo group). Doses could be increased after 6 months if the LIC exceeded 7 mg Fe/g dw and the LIC reduction from baseline was less than 15%. The patients enrolled included 89 males and 77 females. The underlying disease was beta-thalassemia intermedia in 95 (57%) patients, HbE beta-thalassemia in 49 (30%) patients, and alpha-thalassemia in 22 (13%) patients. There were 17 pediatric patients in the study. Caucasians comprised 57% of the study population and Asians comprised 42%. The median baseline LIC (range) for all patients was 12.1 (2.6-49.1) mg Fe/g dw. Follow-up was for 1 year. The primary efficacy endpoint of change in LIC from baseline to Week 52 was statistically significant in favor of both Exjade dose groups compared with placebo (p ≤ 0.001) (Table 5). Furthermore, a statistically significant dose effect of Exjade was observed in favor of the 10 mg/kg/day dose group (10 versus 5 mg/kg/day, p = 0.009). In a descriptive analysis, the target LIC (less than 5 mg Fe/g dw) was reached by 15 (27%) of 55 patients in the 10 mg/kg/day arm, 8 (15%) of 55 patients in the 5 mg/kg/day arm and 2 (4%) of 56 patients in the combined placebo groups.

Study 6 (NCT00873041) was an open-label trial of Exjade for the treatment of patients previously enrolled on Study 5, including cross-over to active treatment for those previously treated with placebo. The starting dose of Exjade in Study 6 was assigned based on the patient’s LIC at completion of Study 5, being 20 mg/kg/day for an LIC exceeding 15 mg Fe/g dw, 10 mg/kg/day for LIC 3-15 mg Fe/g dw, and observation if the LIC was less than 3 mg Fe/g dw. Patients could continue on 5 mg/kg/day if they had previously exhibited at least a 30% reduction in LIC. Doses could be increased to a maximum of 20 mg/kg/day after 6 months if the LIC was more than 7 mg Fe/g dw and the LIC reduction from baseline was less than 15%. The primary efficacy endpoint in Study 6 was the proportion of patients achieving an LIC less than 5 mg Fe/g dw. A total of 133 patients were enrolled. Twenty patients began Study 6 with an LIC less than 5 mg Fe/g dw. Of the 113 patients with a baseline LIC of at least 5 mg Fe/g dw in Study 6, the target LIC (less than 5 mg Fe/g dw) was reached by 39 patients (35%). The responders included 4 (10%) of 39 patients treated at 20 mg/kg/day for a baseline LIC exceeding 15 mg Fe/g dw, and 31 (51%) of 61 patients treated at 10 mg/kg/day for a baseline LIC between 5 and 15 mg Fe/g dw. The absolute change in LIC at Week 52 by starting dose is shown in Table 5 below.

Study 7 (NCT01709838) was an open-label, single-arm, multicenter, 5-year study to evaluate the efficacy and safety of Exjade in iron overloaded patients with NTDT of 10 years of age or older. All patients started treatment on 10 mg/kg/day Exjade for four weeks. At Week 4, dose escalation was based on baseline LIC. At Week 24 and every 6 months thereafter, further dose adjustments were made according to the LIC at that visit. Treatment was interrupted when LIC < 3 mg Fe/g dw or serum ferritin < 300 ng/mL and was restarted at 10 mg/kg/day when LIC ≥ 5 mg Fe/g dw and serum ferritin ≥ 300 ng/mL. Throughout the study, the maximum dose of Exjade given was 30 mg/kg/day.

A total of 134 patients were enrolled in the study. Eligible patients were required to have an LIC of at least 5 mg Fe/g dw measured by R2 MRI and a serum ferritin at least of 300 ng/mL at screening. The mean absolute change of LIC from Baseline to Week 52 was -6.7 mg Fe/g dw. The reduction in LIC was sustained until Week 260 (5 years) with the mean absolute change in LIC from Baseline to Week 260 of -10.6 mg Fe/g dw. In the subset of patients with Baseline LIC > 15 mg Fe/g dw (49 patients), 51.0% achieved a first LIC < 5 mg Fe/g dw (95% CI: 37.5, 64.4) with a median time of 28.6 months. In the subset of patients with target LIC of < 3 mg Fe/g dw (61 patients), 39.3% developed first LIC ≥ 5 mg Fe/g dw in the follow-up period, with a median time of 13.9 months.

Table 5. Absolute Change in LIC at Week 52 in Patients with NTDT
 | Deferasirox Tablets for Oral Suspension Starting Dosea
 | Placebo | 5 mg/kg/day | 10 mg/kg/day | 20 mg/kg/day
Study 5b
Number of Patients | n = 54 | n = 51 | n = 54 | -
Mean LIC at Baseline (mg Fe/g dw) | 16.1 | 13.4 | 14.4 | -
Mean Change (mg Fe/g dw) | +0.4 | -2.0 | -3.8 | -
(95% Confidence Interval) | (-0.6, +1.3) | (-2.9, -1.0) | (-4.8, -2.9) | -
Study 6
Number of Patients | - | n = 8 | n = 77 | n = 43
Mean LIC at Baseline (mg Fe/g dw) | - | 5.6 | 8.8 | 23.5
Mean Change (mg Fe/g dw) | - | -1.5 | -2.8 | -9.1
(95% Confidence Interval) | - | (-3.7, +0.7) | (-3.4, -2.2) | (-11.0, -7.3)
Study 7
Number of Patients | - | - | n = 127 | -
Mean LIC at Baseline (mg Fe/g dw) | - | - | 15.1 | -
Mean Change (mg Fe/g dw) | - | - | -6.7 | -
(95% Confidence Interval) | - | - | (-7.9, -5.5) | -
Abbreviation: LIC, liver iron concentration; NTDT, non-transfusion-dependent thalassemia.
aRandomized dose in Study 5 or assigned starting dose in Study 6 and Study 7.
bLeast square mean change for Study 5.

16 HOW SUPPLIED/STORAGE AND HANDLING

Exjade is provided as 125 mg, 250 mg, and 500 mg tablets for oral suspension.

125 mg

Off-white, round, flat tablet with beveled edge and imprinted with “J” and “125” on one side and “NVR” on the other.

Bottles of 30 tablets………………………………………………………………..(NDC 0078-0468-15)

250 mg

Off-white, round, flat tablet with beveled edge and imprinted with “J” and “250” on one side and “NVR” on the other.

Bottles of 30 tablets………………………………………………………………..(NDC 0078-0469-15)

500 mg

Off-white, round, flat tablet with beveled edge and imprinted with “J” and “500” on one side and “NVR” on the other.

Bottles of 30 tablets………………………………………………………………..(NDC 0078-0470-15)

Store Exjade tablets at 20°C to 25°C (68°F to 77°F); excursions are permitted between 15°C to 30°C (59°F to 86°F) [see USP Controlled Room Temperature]. Protect from moisture.

17 PATIENT COUNSELING INFORMATION

Advise the patient to read the FDA-approved patient labeling (Medication Guide).

Dosing Instructions

Advise patients to take Exjade once daily on an empty stomach at least 30 minutes prior to food, preferably at the same time every day. Instruct patients to completely disperse the tablets in water, orange juice, or apple juice, and drink the resulting suspension immediately. After the suspension has been swallowed, resuspend any residue in a small volume of the liquid and swallow [see Dosage and Administration (2.3)].

Advise patients not to chew tablets or swallow them whole [see Dosage and Administration (2.3)].

Blood Testing

Advise patients that blood tests will be performed frequently to check for damage to kidneys, liver, or blood cells [see Warnings and Precautions (5.1, 5.2, 5.3, 5.4, 5.5)].

Acute Kidney Injury, Including Acute Renal Failure

Caution patients about the potential for kidney toxicity when taking Exjade. Inform patients of the signs and symptoms of kidney injury. Advise patients to contact their healthcare provider immediately if they experience any of these symptoms [see Warnings and Precautions (5.1)].

Hepatic Toxicity and Failure

Caution patients about the potential for hepatic toxicity when taking Exjade. Inform patients of the signs and symptoms of hepatic toxicity. Advise patients to contact their healthcare provider immediately if they experience any of these symptoms [see Warnings and Precautions (5.2)].

GI Ulceration and Hemorrhage

Caution patients about the potential for the development of GI ulcers or bleeding when taking Exjade in combination with drugs that have ulcerogenic or hemorrhagic potential, such as NSAIDs, corticosteroids, oral bisphosphonates, or anticoagulants. Inform patients of the signs and symptoms of GI ulcers or bleeding. Advise patients to contact their health care provider for symptoms of heartburn but to seek immediate medical attention for symptoms of GI hemorrhage [see Warnings and Precautions (5.3)].

Allergic Reactions

Serious allergic reactions (which include swelling of the throat) have been reported in patients taking Exjade, usually within the first month of treatment. If reactions are severe, advise patients to stop taking Exjade immediately and seek immediate medical attention [see Warnings and Precautions (5.7)].

Severe Skin Reactions

Severe skin reactions have been reported in patients taking Exjade. Inform patients of the signs and symptoms of severe skin reactions. If reactions are severe, advise patients to stop taking Exjade immediately and seek immediate medical attention [see Warnings and Precautions (5.8)].

Skin Rash

Skin rashes may occur during Exjade treatment. If the skin rash is severe, advise patients to stop taking Exjade and seek medical attention [see Warnings and Precautions (5.9)].

Pediatric Patients with Acute Illness

Instruct pediatric patients and their caregivers to contact their healthcare provider during episodes of acute illness, especially if the patient has not been drinking fluids or the patient has volume depletion due to fever, vomiting, or diarrhea [see Warnings and Precautions (5.1)].

Auditory and Ocular Testing

Because auditory and ocular disturbances have been reported with Exjade, conduct auditory testing and ophthalmic testing before starting Exjade treatment and thereafter at regular intervals. Advise patients to contact their healthcare provider if they develop visual or auditory changes during treatment [see Warnings and Precautions (5.10)].

Drug Interactions

Caution patients not to take aluminum-containing antacids and Exjade simultaneously [see Drug Interactions (7.1)].

Caution patients about potential loss of effectiveness of drugs metabolized by CYP3A4 (e.g., cyclosporine, simvastatin, hormonal contraceptive agents) when Exjade is administered with these drugs [see Drug Interactions (7.2)].

Caution patients about potential loss of effectiveness of Exjade when administered with drugs that are potent UGT inducers (e.g., rifampicin, phenytoin, phenobarbital, ritonavir). Based on serum ferritin levels and clinical response, consider increases in the dose of Exjade when concomitantly used with potent UGT inducers [see Drug Interactions (7.5)].

Caution patients about potential loss of effectiveness of Exjade when administered with drugs that are bile acid sequestrants (e.g., cholestyramine, colesevelam, colestipol). Based on serum ferritin levels and clinical response, consider increases in the dose of Exjade when concomitantly used with bile acid sequestrants [see Drug Interactions (7.6)].

Caution patients with diabetes to monitor their glucose levels more frequently when repaglinide is used concomitantly with Exjade [see Drug Interactions (7.3)].

Driving and Using Machines

Caution patients experiencing dizziness to avoid driving or operating machinery [see Adverse Reactions (6.1)].

Distributed by:
Novartis Pharmaceuticals Corporation
East Hanover, New Jersey 07936

© Novartis

T2020-105

MEDICATION GUIDE
EXJADE® (ex jayde)
(deferasirox)
tablets
for oral suspension

What is the most important information I should know about Exjade?
Exjade can cause serious side effects, including:
Kidney problems. Exjade can cause sudden (acute) kidney problems, including kidney failure that may require treatment with dialysis, and may cause death. Deaths have happened mostly in people who also have other health problems and had a blood disorder that was in an advanced stage. Adults and children who already have kidney problems and are taking certain medicines with Exjade may also have an increased risk of sudden kidney problems. Be sure to tell your healthcare provider about all the medicines you take during treatment with Exjade.
Your healthcare provider should do blood and urine tests to check your or your child’s kidney function before and during treatment with Exjade. Call your or your child’s healthcare provider right away if:

- your child becomes sick with fever, vomiting, or diarrhea and cannot drink fluids normally during treatment with Exjade. Your child may be dehydrated. Your child’s healthcare provider may need to temporarily stop treatment with Exjade and treat your child for dehydration to help prevent kidney problems. Your child’s healthcare provider may monitor your child’s kidney function more closely.
- you notice that you or your child are passing less urine than usual during treatment with Exjade.

Liver problems. Exjade can cause liver problems, including liver failure that can sometimes cause death. Liver problems with Exjade may be more common in people who are over 55 years of age but can also happen in children. Liver failure has happened more often in people with cirrhosis of the liver and failure of other organs. Liver failure has also happened along with kidney problems in certain children who become dehydrated. See “Kidney problems” above.

Your healthcare provider should do blood tests to check your liver function before you start and regularly during treatment with Exjade. Call your healthcare provider right away, if you develop any of the following signs and symptoms:

- drowsiness
- upper right stomach-area (abdomen) pain

- yellowing or increased yellowing of your skin or eyes,
- dark urine

Bleeding, ulcers, and tears of the stomach or intestine. Severe stomach and intestine bleeding (hemorrhage) that have caused death have happened in some people treated with Exjade, especially in elderly people who have advanced blood cancers or low platelet counts. Some people have also had ulcers of the stomach or intestine, sometimes with tears (perforation) that have caused death. In some people who have taken Exjade, including children and adolescents, irritation of the upper gastrointestinal tract, ulcers, and bleeding have happened, but did not cause death.

Your risk of severe bleeding (hemorrhage) may be increased if you take Exjade along with other medicines that can cause ulcers or bleeding, such as:

- nonsteroidal anti-inflammatory drugs (NSAIDs)
- corticosteroids

- certain osteoporosis medicines called oral bisphosphonates
- blood thinner medicines

Before you start taking Exjade, tell your healthcare provider if you are taking one of these medicines. Ask your healthcare provider if you are not sure. If you develop an ulcer of the stomach or intestine, or severe bleeding, your healthcare provider may stop Exjade.

Elderly people may be at a higher risk of developing serious side effects and death due to serious side effects with Exjade. Your healthcare provider may need to monitor you more closely during treatment with Exjade.

- Tell your healthcare provider if you get heartburn during treatment with Exjade.
- Get emergency medical help right away if you vomit blood or pass black or bloody stools, or if you have severe stomach-area (abdomen) pain during treatment with Exjade.

See "What are the possible side effects of Exjade?" for more information about side effects.

What is Exjade?
Exjade is a prescription medicine that is used to treat:

- people 2 years of age and older who have an increased amount of iron in their blood for a long period of time (chronic), caused by repeated blood transfusions
- certain people 10 years of age or older with thalassemia who have an increased amount of iron in their blood but who are not receiving regular blood transfusions

It is not known if Exjade is safe and effective when used with other medicines to treat an increased amount of iron in the blood.

It is not known if Exjade is safe and effective for treating children under 2 years of age who have an increased amount of iron in their blood for a long period of time (chronic) caused by repeated blood transfusions.

It is not known if Exjade is safe and effective for treating children under 10 years of age with thalassemia who have an increased amount of iron in their blood, but who are not receiving regular blood transfusions.

Do not take Exjade if you:

- have certain kidney problems
- have high-risk myelodysplastic syndrome (MDS)
- have advanced cancer
- have a low platelet count
- are allergic to deferasirox or any of the ingredients in Exjade. See the end of this Medication Guide for a list of the ingredients in Exjade.

Ask your healthcare provider if you are not sure if you have any of the medical conditions listed above.

Before taking Exjade, tell your healthcare provider about all of your medical conditions, including if you:

- have kidney problems
- have liver problems
- have advanced cancer. See “Do not take Exjade if you”
- have a blood disorder that may increase your risk for bleeding
- are pregnant or plan to become pregnant. It is not known if Exjade can harm your unborn baby. Hormonal forms of birth control may not be as effective if used during treatment with Exjade. You could become pregnant. Talk to your healthcare provider about other birth control options that you can use during this time. Tell your healthcare provider right away if you become pregnant during treatment with Exjade.
- are breastfeeding or plan to breastfeed. It is not known if Exjade passes into your breast milk and can harm your baby. You and your healthcare provider should decide if you will take Exjade or breastfeed. You should not do both.

Tell your healthcare provider about all the medicines you take, including prescription medicines, over-the-counter medicines, vitamins, and herbal supplements. Some medicines may affect how Exjade works, and Exjade may affect how other medicines work. Also, your risk of sudden kidney problems or severe bleeding may be increased if you take Exjade with certain medicines. See “What is the most important information I should know about Exjade?”

- Avoid taking the following medicines during treatment with Exjade:
  - antacid products (medicines used to treat heartburn) that contain aluminum
  - theophylline
  - certain medicines to lower your cholesterol, called bile acid sequestrants.

Ask your healthcare provider if you are not sure if you take one of these medicines.

Know the medicines you take. Keep a list of them to show your healthcare provider or pharmacist when you get a new medicine.

How should I take Exjade?

- Take Exjade exactly as your healthcare provider tells you to.
- Do not change your dose of Exjade or stop taking it unless your healthcare provider tells you to.
- Take Exjade 1 time every day, preferably at the same time every day.
- Take Exjade on an empty stomach at least 30 minutes before eating food.
- Do not chew Exjade tablets or swallow them whole.
- Place the prescribed number of Exjade tablets in a cup with water, orange juice, or apple juice. Stir to disperse the tablets in the liquid.
  - If your prescribed dose of Exjade is less than 1 gram, use 3.5 ounces of liquid to disperse the tablets.
  - If your prescribed dose of Exjade is 1 gram or more, use 7 ounces of liquid to disperse the tablets.
- Completely disperse the tablets until it becomes a fine suspension. Then drink the suspension right away.
- Do not disperse Exjade tablets in carbonated drinks or milk.
- After drinking the suspension, add a small amount of water, orange juice, or apple juice to the cup to disperse any remaining medicine, and then drink it.
- Do not take Exjade with aluminum-containing antacid products. See “Before taking Exjade.”
- Tell your healthcare provider if you or your child gain or lose any weight. Your or your child’s dose of Exjade may need to be adjusted.
- If you take the diabetes medicine repaglinide during treatment with Exjade, you may need to test your blood sugar (glucose) levels more often. Follow your healthcare provider’s instructions about how often to test your blood sugar during this time.
- Your healthcare provider should do blood and urine tests before, and during treatment to check how you respond to Exjade, and to monitor you for side effects. Your healthcare provider may change your dose, or temporarily or permanently stop Exjade if you have certain side effects.
- In people who have thalassemia, your healthcare provider will check the amount of iron in your liver before and during treatment with Exjade.
- If you or your child take too much Exjade, call your healthcare provider right away or go to the nearest hospital emergency room. Symptoms that can happen if you take too much Exjade include: stomach-area (abdominal) pain, diarrhea, nausea, and vomiting.

What should I avoid while taking Exjade?

- Exjade may cause dizziness. Avoid driving or operating machinery until you know how Exjade affects you. Do not drive or operate machinery if Exjade makes you dizzy.

What are the possible side effects of Exjade?
Exjade can cause serious side effects, including:

- See "What is the most important information I should know about Exjade?"
- Effects on your bone marrow. Exjade can affect your bone marrow and cause you to have a low white blood cell count which can be serious, decreased platelets, or worsening of your anemia, and may lead to death. Your risk for effects on your bone marrow may be increased if you already have other blood disorders. Your healthcare provider will do blood tests to monitor your blood cell counts for these problems.
- Serious allergic reactions. Exjade may cause serious allergic reactions, which usually start within the first month of treatment. Get medical help right away if you develop any of the following symptoms of a serious allergic reaction including:

- difficulty in breathing or swallowing
- chest pain
- rapid heartbeat
- feeling faint

- swelling of the face, lips, mouth, tongue or throat
- severe itching of the skin with a red rash or raised bumps
- hives

- Skin rash and severe skin reactions. Skin rashes are common with Exjade. If you get a more severe rash, your healthcare provider may temporarily stop Exjade.

Severe skin reactions can also happen with Exjade and can be life-threatening or lead to death. Get medical help right away if you develop any one or more of the following signs and symptoms of a severe skin reaction, including:

- rash or red skin
- blisters on your lips, or around your mouth or eyes
- mouth sores

- skin peeling
- high fever or flu-like symptoms
- enlarged lymph nodes

- Hearing and vision problems. Exjade can cause decreased hearing and changes in your vision, including cataracts, increased pressure in your eye, and problems with your retinas. Your healthcare provider should do hearing and vision tests before you start and then regularly during treatment. Your healthcare provider may decrease your dose or stop Exjade if you develop hearing or vision problems.

Tell your healthcare provider if you develop any changes in your vision or hearing during treatment with Exjade.

The most common side effects in anyone who takes Exjade include: diarrhea and nausea.

Other common side effects in people with too much iron in their blood due to repeated blood transfusions include: vomiting, stomach-area (abdomen) pain, and an abnormal kidney function blood test.

These are not all the possible side effects of Exjade.

Call your doctor for medical advice about side effects. You may report side effects to FDA at 1-800-FDA-1088.

How should I store Exjade?

- Store Exjade at room temperature between 68°F to 77°F (20°C to 25°C).
- Keep the bottle closed tightly and away from moisture.

Keep Exjade and all medicines out of the reach of children.

General information about the safe and effective use of Exjade.

Medicines are sometimes prescribed for purposes other than those listed in a Medication Guide. Do not use Exjade for a condition for which it was not prescribed. Do not give Exjade to other people, even if they have the same symptoms that you have. It may harm them. You can ask your pharmacist or healthcare provider for information about Exjade that is written for health professionals.

What are the ingredients in Exjade?
Active ingredient: deferasirox
Inactive ingredients: Crospovidone, lactose monohydrate, magnesium stearate, microcrystalline cellulose, povidone (K30), silicone dioxide, and sodium lauryl sulphate.

Distributed by: Novartis Pharmaceuticals Corporation, East Hanover, New Jersey 07936

For more information, go to www.EXJADE.com or call 1-888-669-6682

© Novartis

This Medication Guide has been approved by the U.S. Food and Drug Administration.

Revised: July 2020

T2020-106

PRINCIPAL DISPLAY PANEL

NDC 0078-0468-15 Rx only

EXJADE®
(deferasirox)

Tablets for Oral Suspension*

125 mg per tablet

PHARMACIST: Dispense with accompanying
Medication Guide to each patient.

DO NOT CHEW OR SWALLOW WHOLE

*Tablets MUST be dispersed in water,

orange or apple juice prior to ingestion.

NOVARTIS 30 Tablets

PRINCIPAL DISPLAY PANEL

NDC 0078-0469-15 Rx only

EXJADE®
(deferasirox)

Tablets for Oral Suspension*

250 mg per tablet

PHARMACIST: Dispense with accompanying
Medication Guide to each patient.

DO NOT CHEW OR SWALLOW WHOLE

*Tablets MUST be dispersed in water,

orange or apple juice prior to ingestion.

NOVARTIS 30 Tablets

PRINCIPAL DISPLAY PANEL

NDC 0078-0470-15 Rx only

EXJADE®
(deferasirox)

Tablets for Oral Suspension*

500 mg per tablet

PHARMACIST: Dispense with accompanying
Medication Guide to each patient.

DO NOT CHEW OR SWALLOW WHOLE

*Tablets MUST be dispersed in water,

orange or apple juice prior to ingestion.

NOVARTIS 30 Tablets